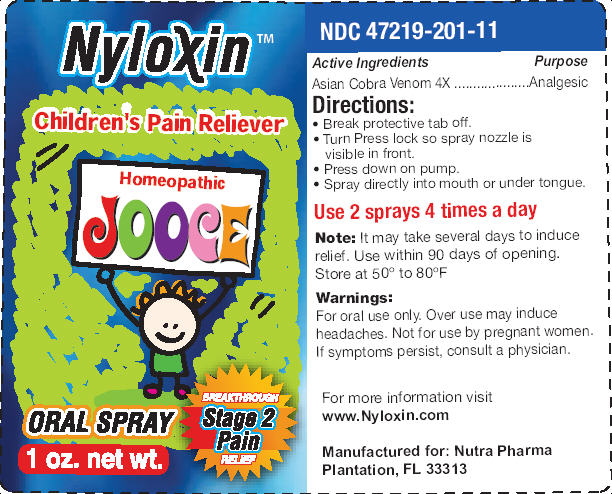 DRUG LABEL: NYLOXIN
NDC: 47219-203 | Form: SPRAY, METERED
Manufacturer: RECEPTOPHARM INC
Category: homeopathic | Type: HUMAN OTC DRUG LABEL
Date: 20091130

ACTIVE INGREDIENTS: NAJA NAJA VENOM .035 mg/1 mL
INACTIVE INGREDIENTS: ANHYDROUS CITRIC ACID; ANHYDROUS TRISODIUM CITRATE; METHYLPARABEN; XYLITOL; 2-(DIETHYLAMINO)ETHANOL

DRUG FACTS

Active Ingredients

Asian Cobra venom 4X

Purpose

Analgesic

Directions:

- Break protective tab off.
- Turn Press lock so spray nozzle is visible in front.
- Press down on pump.
- Spray directly into mouth or under tongue.

Use 2 sprays 4 times a day

Note: It may take several days to induce relief. Use within 90 days of opening.
Store at 50° to 80°F

Warnings:

For oral use only. Over use may induce headaches. Not for use by pregnant women. If symptoms persist, consult a physician.

For more information visit
www.Nyloxin.com
Manufactured for: Nutra Pharma
Plantation, FL 33313

PACKAGE LABEL

Package Label - Principal Display Panel – 0.5 oz Spray Label